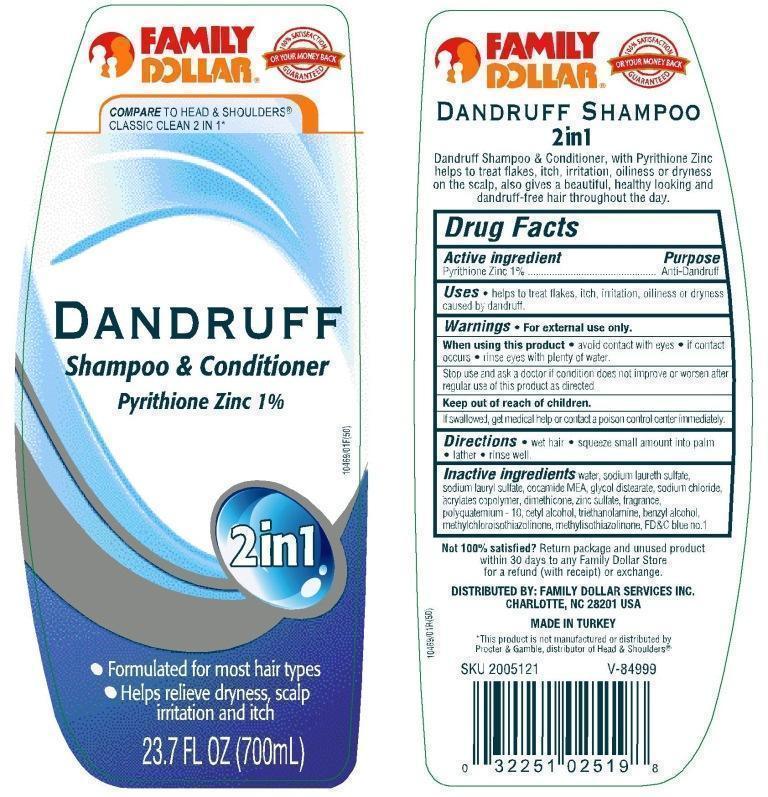 DRUG LABEL: 2in1
NDC: 55319-154 | Form: SHAMPOO
Manufacturer: Family Dollar
Category: otc | Type: HUMAN OTC DRUG LABEL
Date: 20120716

ACTIVE INGREDIENTS: PYRITHIONE ZINC 1 mL/100 mL
INACTIVE INGREDIENTS: WATER; SODIUM LAURETH SULFATE; SODIUM LAURYL SULFATE; COCO MONOETHANOLAMIDE; GLYCOL DISTEARATE; SODIUM CHLORIDE; DIMETHICONE; ZINC SULFATE; POLYQUATERNIUM-10 (400 CPS AT 2%); CETYL ALCOHOL; TROLAMINE; BENZYL ALCOHOL; METHYLCHLOROISOTHIAZOLINONE; METHYLISOTHIAZOLINONE; FD&C BLUE NO. 1

DRUG FACTS

Active Ingredient
Pyrithione zinc 1%

Purpose
Anti-dandruff

INDICATIONS AND USAGE

Uses • helps to treat flakes, itch, irritation, oilness or dryness caused by dandruff.

Warnings
For external use only

When using this product •avoid contact with eyes • if contact occurs, rinse eyes with plenty of water.

Stop use and ask a doctor if condition does not improve or worsen after regular use of this product as directed

KEEP OUT OF REACH OF CHILDREN

Keep this and all drugs out of reach of children If swallowed get medical help or contact a Poison Control Center right away.

DOSAGE AND ADMINISTRATION

Directions •wet hair, •squeeze small amount into palm •lather, •rinse well

INACTIVE INGREDIENT

Inactive Ingredients water, sodium laureth sulfate, sodium lauryl sulfate, cocamide MEA, glycol distearate, sodium chloride, acrylates copolymer, dimethicone, zinc sulfate, fragrance, polyquaterinum-10, cetyl alcohol, triethanolamine, benzyl alcohol, methylchloroisothiazolinone, methylisothiazolinone, FDC blue no.1

package label